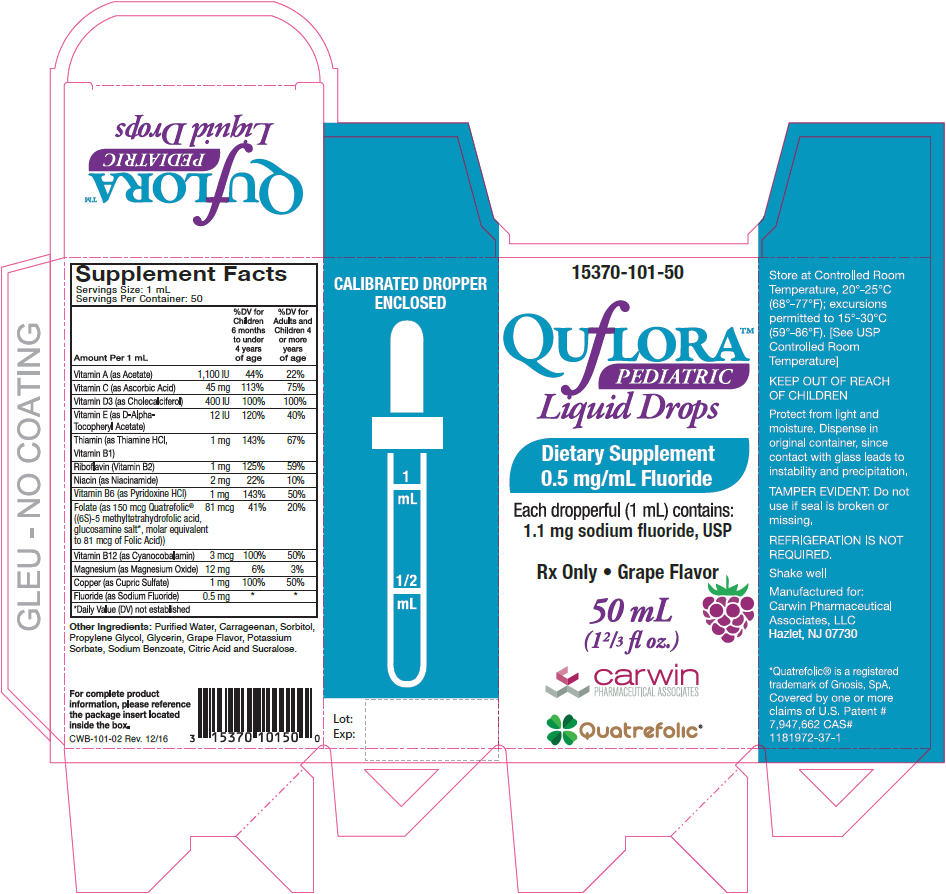 DRUG LABEL: Quflora Pediatric Drops
NDC: 15370-101 | Form: LIQUID
Manufacturer: CarWin Pharmaceutical Associates, LLC
Category: prescription | Type: HUMAN PRESCRIPTION DRUG LABEL
Date: 20170803

ACTIVE INGREDIENTS: VITAMIN A ACETATE 1100 [iU]/1 mL; ASCORBIC ACID 45 mg/1 mL; CHOLECALCIFEROL 400 [iU]/1 mL; .ALPHA.-TOCOPHEROL ACETATE, D- 12 [iU]/1 mL; THIAMINE HYDROCHLORIDE 1 mg/1 mL; RIBOFLAVIN 1 mg/1 mL; NIACINAMIDE 2 mg/1 mL; PYRIDOXINE HYDROCHLORIDE 1 mg/1 mL; LEVOMEFOLIC ACID 81 ug/1 mL; CYANOCOBALAMIN 3 ug/1 mL; MAGNESIUM OXIDE 12 mg/1 mL; CUPRIC SULFATE 1 mg/1 mL; SODIUM FLUORIDE 0.5 mg/1 mL
INACTIVE INGREDIENTS: CARRAGEENAN; CITRIC ACID MONOHYDRATE; GRAPE; POTASSIUM SORBATE; SUCRALOSE; WATER

Quatrefolic® 0.5 mg/mL F* Pediatric Fluoride Drops

Supplement Facts
Serving Size: 1 mL
Servings Per Container: 50
Amount Per 1 mL |  | % Daily Value Children 6 months to under 4 years of age | % Daily Value for Adults and Children 4 or more years of age
Vitamin A (as Acetate) | 1,100 IU | 44% | 22%
Vitamin C (as Ascorbic Acid) | 45 mg | 113% | 75%
Vitamin D3 (as Cholecalciferol) | 400 IU | 100% | 100%
Vitamin E (as D-Alpha-Tocopheryl Acetate) | 12 IU | 120% | 40%
Thiamin (as Thiamine HCl, Vitamin B1) | 1 mg | 143% | 67%
Riboflavin (Vitamin B2) | 1 mg | 125% | 59%
Niacin (as Niacinamide) | 2 mg | 22% | 10%
Vitamin B6 (as Pyridoxine HCl) | 1 mg | 143% | 50%
Folate (as 150 mcg Quatrefolic® ((6S)-5-methyltetrahydrofolic acid, glucosamine salt [Daily Value (DV) not established] , molar equivalent to 81 mcg of Folic Acid)) | 81 mcg | 41% | 20%
Vitamin B12 (as Cyanocobalamin) | 3 mcg | 100% | 50%
Magnesium (as Magnesium Oxide) | 12 mg | 6% | 3%
Copper (as Cupric Sulfate) | 1 mg | 100% | 50%
Fluoride (as Sodium Fluoride) | 0.5 mg

Other Ingredients: Purified Water, Carrageenan, Sorbitol, Propylene Glycol, Glycerin, Grape Flavor, Potassium Sorbate, Sodium Benzoate, Citric Acid and Sucralose.

INDICATIONS AND USAGE

Quflora® 0.5 mg/mL F* Pediatric Drops is a prescription dietary supplement providing essential vitamins, minerals and fluoride.

CONTRAINDICATIONS

Do not use in areas where drinking water exceeds 0.6 ppm F. Do not administer to pediatric patients less than 6 months old

PRECAUTIONS

General

Do not use this product if you are allergic to any of the ingredients. The suggested dose should not be exceeded, since dental fluorosis may result from continued ingestion of large amounts of fluoride. Do not eat or drink dairy products within one hour of fluoride administration since these may decrease effectiveness.

Folic Acid

Folic Acid alone is improper therapy in the treatment of pernicious anemia and other megaloblastic anemias where vitamin B12 is deficient. Folic acid in doses above 0.1 mg daily may obscure pernicious anemia in that hematologic remission can occur while neurological manifestations progress.

Other information

Call your doctor for medical advice about side effects. You may report serious side effects by calling Carwin Pharmaceutical Associates, LLC at 1-844-700-5011.

WARNINGS

Keep out of the reach of children. In case of accidental overdose, seek professional emergency assistance or contact a Poison Control Center immediately.

DOSAGE AND ADMINISTRATION

See schedule below to determine dosage. Administer orally as prescribed by a healthcare practitioner. Use with calibrated dropper for measuring doses.

Fluoride Ion Level In Drinking Water (ppm) [1.0 part per million (ppm) = 1 milligram/liter (mg/L)]
Age | Less than 0.3ppm | 0.3-0.6 ppm | Greater than 0.6 ppm
Birth-6 months | None | None | None
6 months-3 years | 0.25 mg/day [2.2 mg sodium fluoride contains 1 mg fluoride ion] | None | None
3-6 years | 0.50 mg/day | 0.25 mg/day | None
6-16 years | 1.0 mg/day | 0.50 mg/day | None

Dietary Fluoride Supplement dosing schedule approved by the American Dental Association (ADA), American Academy of Pediatrics (AAP) & American Academy of Pediatric Dentistry (AAPD).

DESCRIPTION

Quflora® 0.5 mg/mL F* Pediatric Drops is a light brown, dye free, grape flavored liquid.

HOW SUPPLIED

Quflora® 0.5 mg/mL F* Pediatric Drops in 50 mL (1 2/3 FL. OZ.) child-resistant bottles with accompanying calibrated dropper (Product Code: 15370-101-50).

Rx Only

STORAGE

Store at controlled room temperature 20°C to 25°C (68°F to 77°F). Protect from light, moisture and heat.

SHAKE BEFORE USING

TAMPER EVIDENT: Do not use if seal is broken or missing.

Quatrefolic® is a registered trademark of Gnosis, SpA. Covered by one or more claims of U.S. Patent # 7,947,662 CAS# 1181972-37-1

Manufactured for:
Carwin Pharmaceutical Associates, LLC
Hazlet, NJ 07730

CAR-101-02
Rev. 5/17

PRINCIPAL DISPLAY PANEL - 50 mL Bottle Carton

15370-101-50

QUfLORA™
PEDIATRIC
Liquid Drops

Dietary Supplement
0.5 mg/mL Fluoride

Each dropperful (1 mL) contains:
1.1 mg sodium fluoride, USP

Rx Only • Grape Flavor

50 mL
(1⅔ fl oz.)

carwin
PHARMACEUTICAL ASSOCIATES

Quatrefolic®